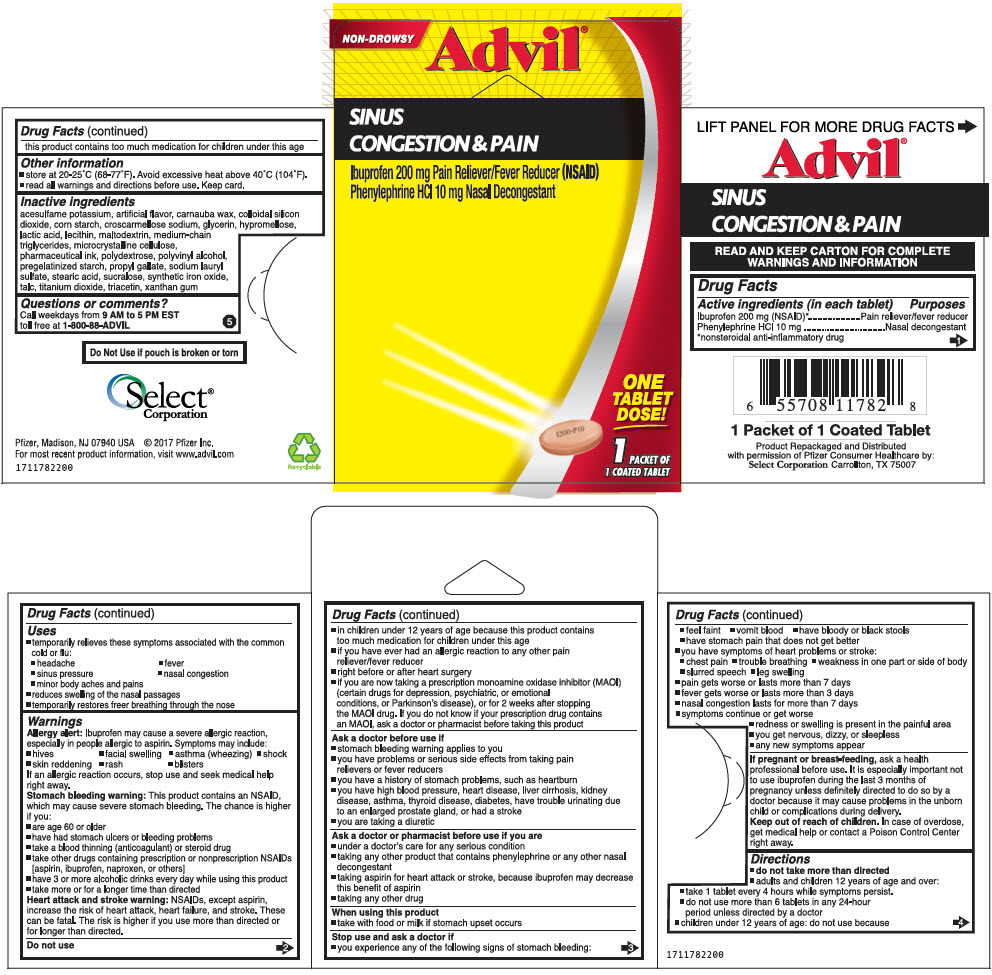 DRUG LABEL: Advil Sinus Congestion and Pain
NDC: 52904-782 | Form: TABLET, COATED
Manufacturer: Select Corporation
Category: otc | Type: HUMAN OTC DRUG LABEL
Date: 20220412

ACTIVE INGREDIENTS: Ibuprofen 200 mg/1 1; PHENYLEPHRINE HYDROCHLORIDE 10 mg/1 1
INACTIVE INGREDIENTS: acesulfame potassium; carnauba wax; silicon dioxide; STARCH, CORN; croscarmellose sodium; glycerin; hypromellose, unspecified; lactic acid, unspecified form; egg phospholipids; maltodextrin; medium-chain triglycerides; microcrystalline cellulose; polydextrose; polyvinyl alcohol, unspecified; propyl gallate; sodium lauryl sulfate; stearic acid; sucralose; ferric oxide red; talc; titanium dioxide; triacetin; xanthan gum

Advil® Sinus Congestion & Pain

Drug Facts

ACTIVE INGREDIENT

PURPOSE

Active ingredients (in each tablet) | Purposes
Ibuprofen 200 mg (NSAID) [nonsteroidal anti-inflammatory drug] | Pain reliever/fever reducer
Phenylephrine HCl 10 mg | Nasal decongestant

Uses

- temporarily relieves these symptoms associated with the common cold or flu:
  - headache
  - fever
  - sinus pressure
  - nasal congestion
  - minor body aches and pains
- reduces swelling of the nasal passages
- temporarily restores freer breathing through the nose

Warnings

Allergy alert

Ibuprofen may cause a severe allergic reaction, especially in people allergic to aspirin. Symptoms may include:

- hives
- facial swelling
- asthma (wheezing)
- shock
- skin reddening
- rash
- blisters

If an allergic reaction occurs, stop use and seek medical help right away.

Stomach bleeding warning

This product contains an NSAID, which may cause severe stomach bleeding. The chance is higher if you:

- are age 60 or older
- have had stomach ulcers or bleeding problems
- take a blood thinning (anticoagulant) or steroid drug
- take other drugs containing prescription or nonprescription NSAIDs [aspirin, ibuprofen, naproxen, or others]
- have 3 or more alcoholic drinks every day while using this product
- take more or for a longer time than directed

Heart attack and stroke warning

NSAIDs, except aspirin, increase the risk of heart attack, heart failure, and stroke. These can be fatal. The risk is higher if you use more than directed or for longer than directed.

Do not use

- in children under 12 years of age because this product contains too much medication for children under this age
- if you have ever had an allergic reaction to any other pain reliever/fever reducer
- right before or after heart surgery
- if you are now taking a prescription monoamine oxidase inhibitor (MAOI) (certain drugs for depression, psychiatric, or emotional conditions, or Parkinson's disease), or for 2 weeks after stopping the MAOI drug. If you do not know if your prescription drug contains an MAOI, ask a doctor or pharmacist before taking this product

Ask a doctor before use if

- stomach bleeding warning applies to you
- you have problems or serious side effects from taking pain relievers or fever reducers
- you have a history of stomach problems, such as heartburn
- you have high blood pressure, heart disease, liver cirrhosis, kidney disease, asthma, thyroid disease, diabetes, have trouble urinating due to an enlarged prostate gland, or had a stroke
- you are taking a diuretic

Ask a doctor or pharmacist before use if you are

- under a doctor's care for any serious condition
- taking any other product that contains phenylephrine or any other nasal decongestant
- taking aspirin for heart attack or stroke, because ibuprofen may decrease this benefit of aspirin
- taking any other drug

When using this product

- take with food or milk if stomach upset occurs

Stop use and ask a doctor if

- you experience any of the following signs of stomach bleeding:
  - feel faint
  - vomit blood
  - have bloody or black stools
  - have stomach pain that does not get better
- you have symptoms of heart problems or stroke:
  - chest pain
  - trouble breathing
  - weakness in one part or side of body
  - slurred speech
  - leg swelling
- pain gets worse or lasts more than 7 days
- fever gets worse or lasts more than 3 days
- nasal congestion lasts for more than 7 days
- symptoms continue or get worse
- redness or swelling is present in the painful area
- you get nervous, dizzy, or sleepless
- any new symptoms appear

PREGNANCY OR BREAST FEEDING

If pregnant or breast-feeding, ask a health professional before use. It is especially important not to use ibuprofen during the last 3 months of pregnancy unless definitely directed to do so by a doctor because it may cause problems in the unborn child or complications during delivery.

Keep out of reach of children. In case of overdose, get medical help or contact a Poison Control Center right away.

Directions

- do not take more than directed
- adults and children 12 years of age and over:
  - take 1 tablet every 4 hours while symptoms persist.
  - do not use more than 6 tablets in any 24-hour period unless directed by a doctor
- children under 12 years of age: do not use because this product contains too much medication for children under this age

Other information

- store at 20-25°C (68-77°F). Avoid excessive heat above 40°C (104°F).
- read all warnings and directions before use. Keep card.

Inactive ingredients

acesulfame potassium, artificial flavor, carnauba wax, colloidal silicon dioxide, corn starch, croscarmellose sodium, glycerin, hypromellose, lactic acid, lecithin, maltodextrin, medium-chain triglycerides, microcrystalline cellulose, pharmaceutical ink, polydextrose, polyvinyl alcohol, pregelatinized starch, propyl gallate, sodium lauryl sulfate, stearic acid, sucralose, synthetic iron oxide, talc, titanium dioxide, triacetin, xanthan gum

Questions or comments?

Call weekdays from 9 AM to 5 PM EST toll free at 1-800-88-ADVIL

Product Repackaged and Distributed
with permission of Pfizer Consumer Healthcare by:
Select Corporation Carrollton, TX 75007

PRINCIPAL DISPLAY PANEL - 1 Tablet Pouch Blister Pack

NON-DROWSY

Advil®

SINUS
CONGESTION & PAIN

Ibuprofen 200 mg Pain Reliever/Fever Reducer (NSAID)
Phenlephrine HCl 10 mg Nasal Decongestant

ONE
TALBET
DOSE!

1 PACKET OF
1 COATED TABLET